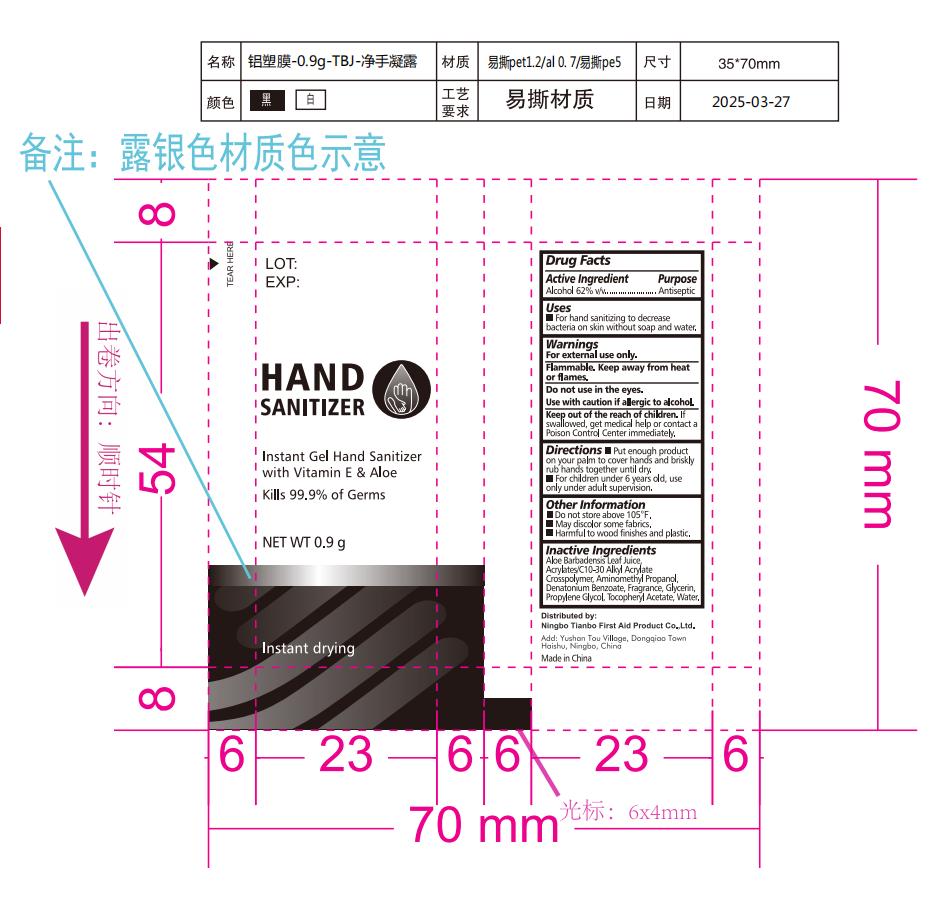 DRUG LABEL: HAND SANITIZER
NDC: 73288-008 | Form: GEL
Manufacturer: NINGBO TIANBO FIRST AID PRODUCT CO., LTD.
Category: otc | Type: HUMAN OTC DRUG LABEL
Date: 20250419

ACTIVE INGREDIENTS: ALCOHOL 62 mL/100 mL
INACTIVE INGREDIENTS: WATER; GLYCERIN; PROPYLENE GLYCOL; ACRYLATES/C10-30 ALKYL ACRYLATE CROSSPOLYMER (60000 MPA.S); .ALPHA.-TOCOPHEROL ACETATE, D-; DENATONIUM BENZOATE; ALOE VERA LEAF; AMINOMETHYL PROPANEDIOL

73288-008 Hand Sanitizer

Active ingredient

Alcohol 62% v/v

Purpose Antiseptic

Uses

For hand sanitizing to decrease bacteria on skin without soap and water

Warnings

For external use only.

Flammable: keep away from heat or flame

Do not use in the eyes

Use with caution if allergic to alcohol

Keep out of reach of children. If product is swallowed, get medical help or contact a Poison Control Center right away.

Directions:

Put enough product on your palm to cover hands and briskly rub hands until dry
Wet hands thoroughly with product and allow to dry without wiping

- For children under 6, use only under adult supervision.

Other information

- Do not store above 105 F
- May discolor some fabrics
- Harmful to wood finishes and plastics

Inactive ingredients

Acrylates/C10-30Alkyl Acrylate Crosspolymer, Aminomethyl Propanol, Aloe Barbadensis Leaf Juice, Denatonium Benzoate, Fragrance, Glycerin, Propylene Glycol, Tocopheryl Acetate, Water (Aqua).